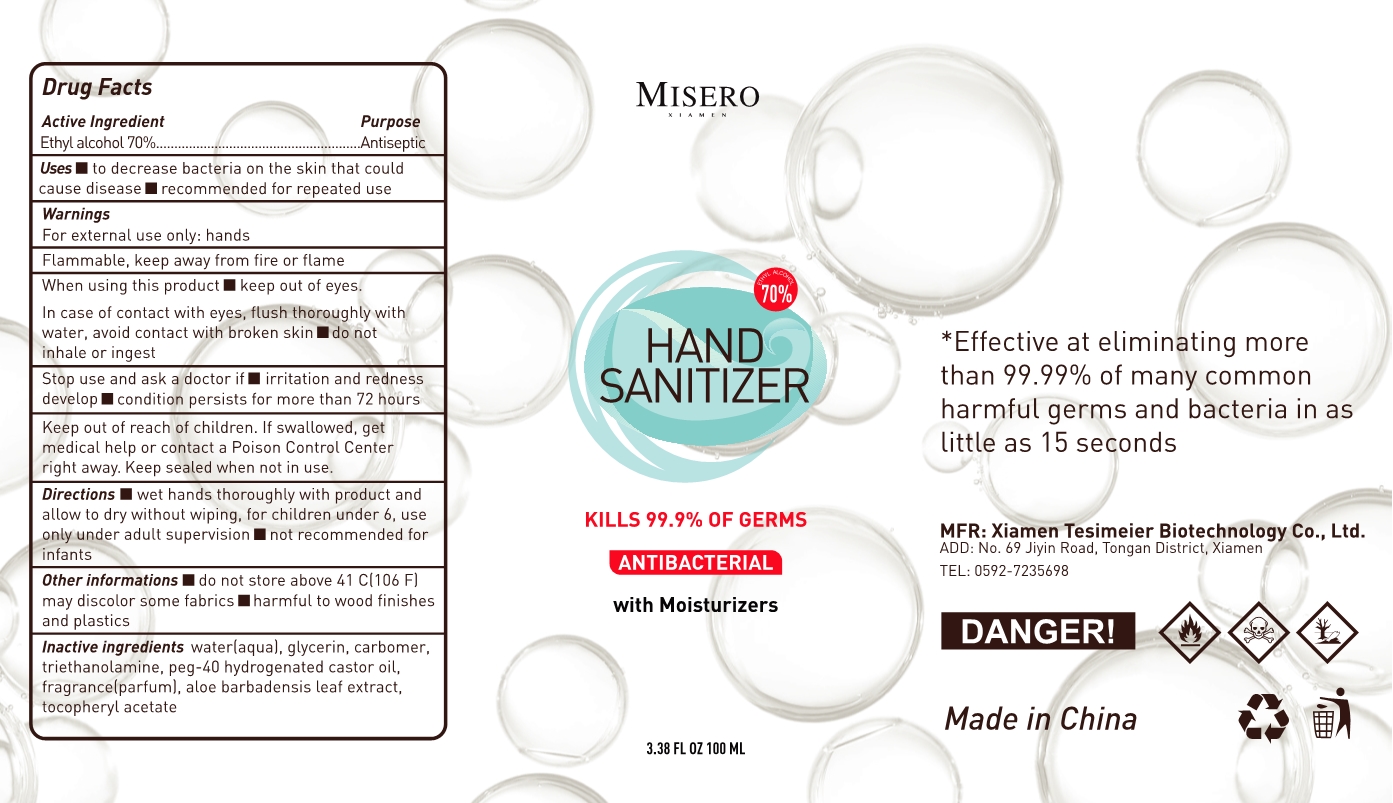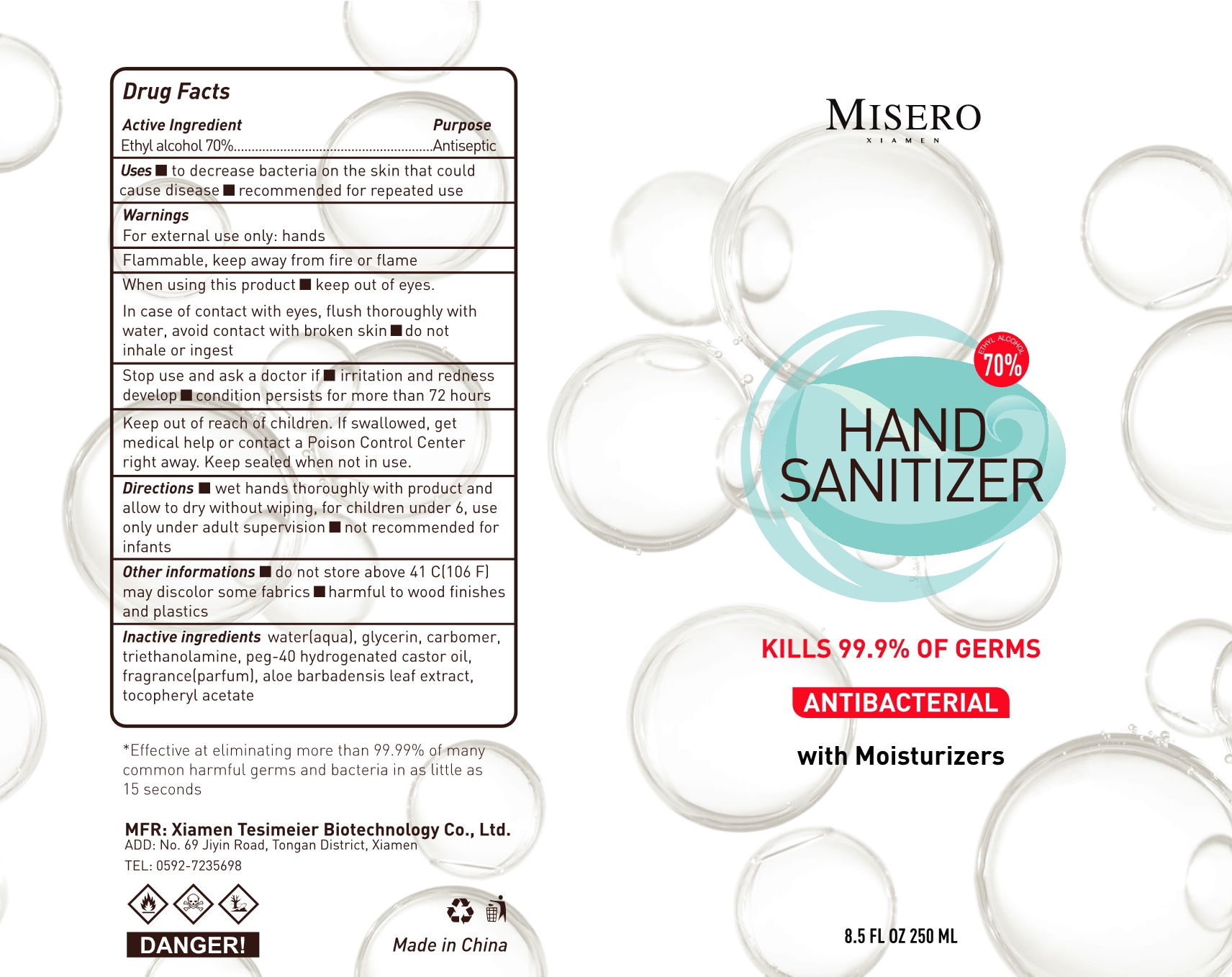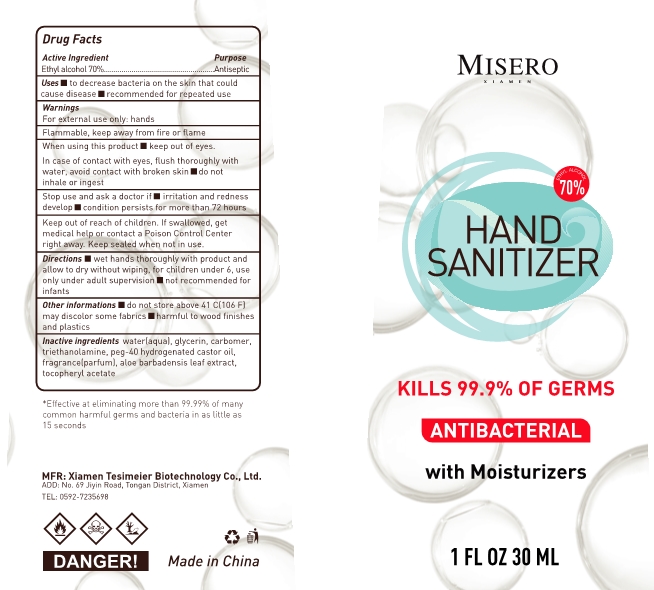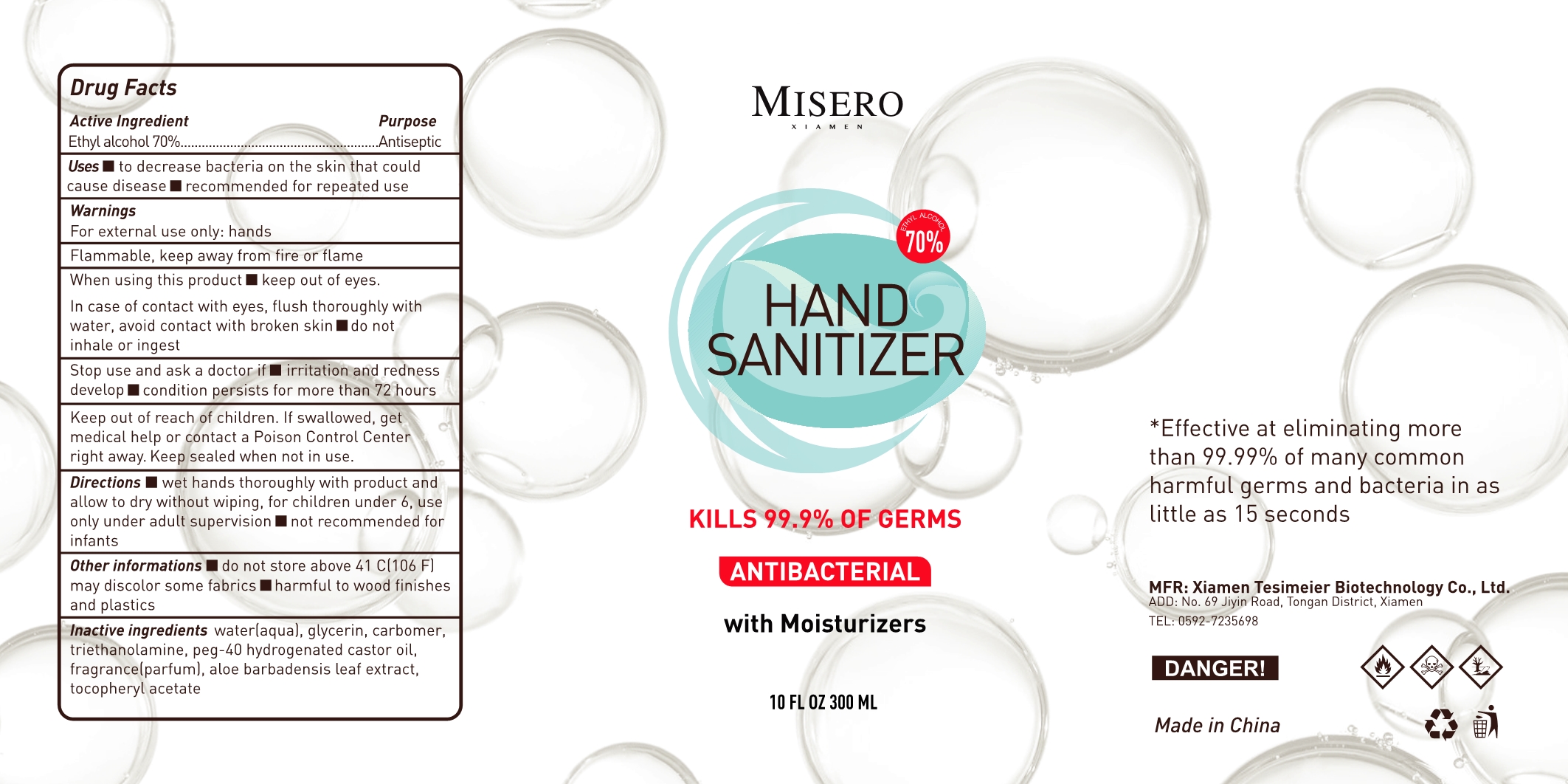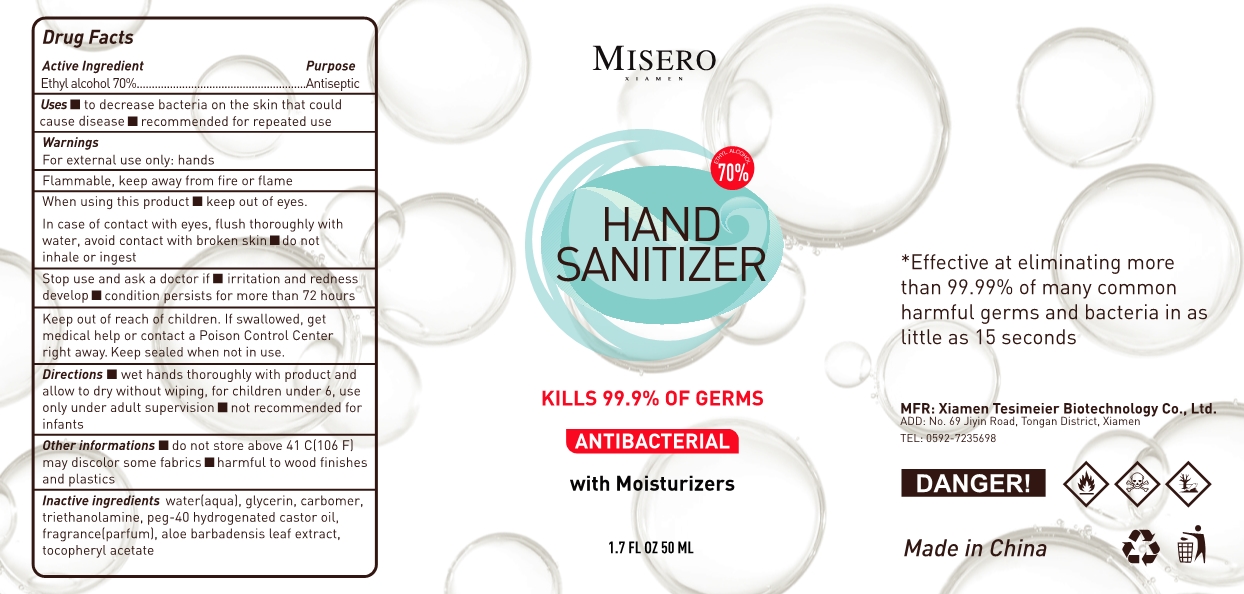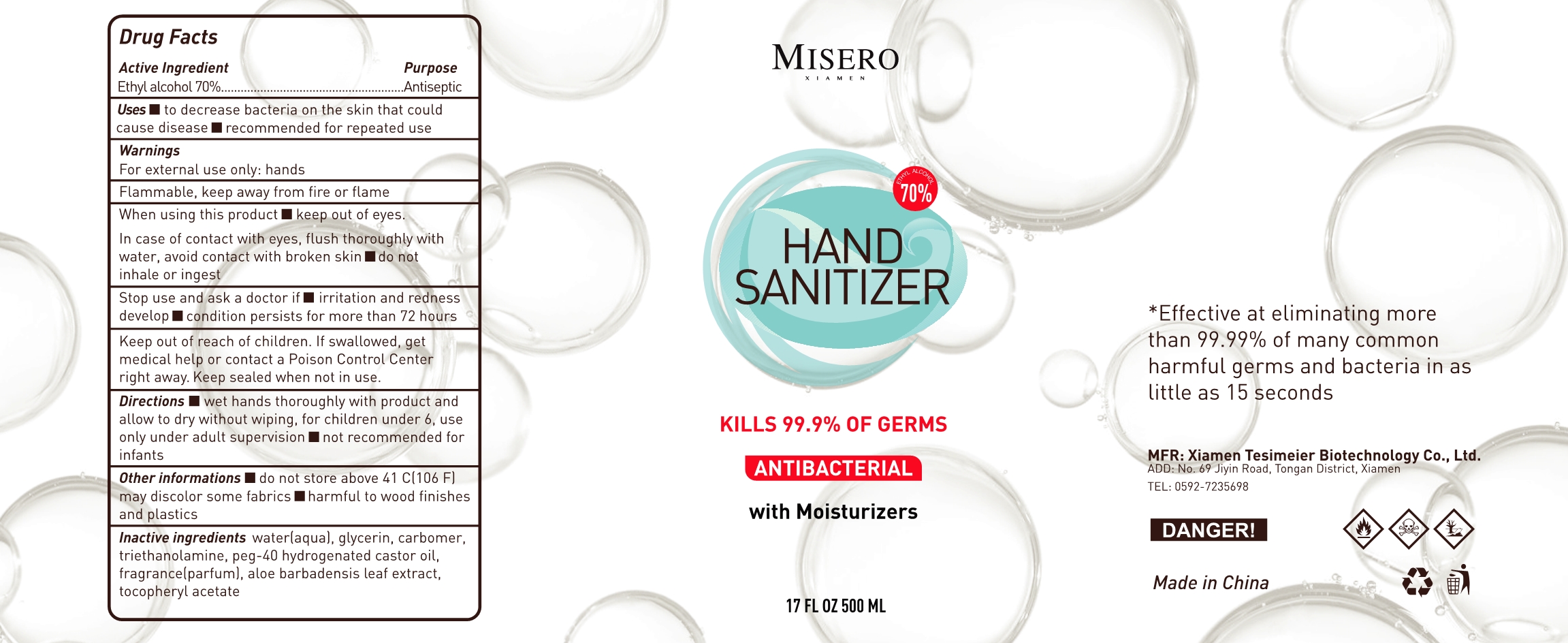 DRUG LABEL: HAND SANITIZER
NDC: 75606-001 | Form: GEL
Manufacturer: Xiamen Tesimeier Biotechnology Co., Ltd.
Category: otc | Type: HUMAN OTC DRUG LABEL
Date: 20200616

ACTIVE INGREDIENTS: ALCOHOL 70 mL/100 mL
INACTIVE INGREDIENTS: GLYCERIN; CARBOMER 1342; WATER; TROLAMINE; FRAGRANCE LAVENDER & CHIA F-153480; ALOE VERA LEAF; POLYOXYL 40 HYDROGENATED CASTOR OIL; .ALPHA.-TOCOPHEROL ACETATE

HAND SANITIZER

Active Ingredient(s)

Ethyl alcohol 70%

Purpose

Antiseptic

Use

to decrease bacteria on the skin that could cause disease
recommended for repeated use

Warnings

For external use only: hands
Flammable, keep away from fire or flame

Do not use

/

When using this product
keep out of eyes
In case of contact with eyes, flush thoroughly with water. avoid contact with broken skin
do not inhale or ingest

Stop use and ask a doctor if
irritation and redness develop
condition persists for more than 72 hours

Keep out of reach of children. If swallowed, get medical help or contact a Poison Control Center right away. Keep sealed when not in use

Directions

wet hands thoroughly with product and allow to dry without wiping, for children under 6, use only under adult supervision
not recommended for infants

Other information

do not store above 41 C(106 F) may discolor some fabrics harmful to wood finishes and plastics

Inactive ingredients

water(aqua), glycerin, carbomer, triethanolamine, peg-40 hydrogenated castor oil, fragrance(parfum), aloe barbadensis leaf extract, tocopheryl acetate